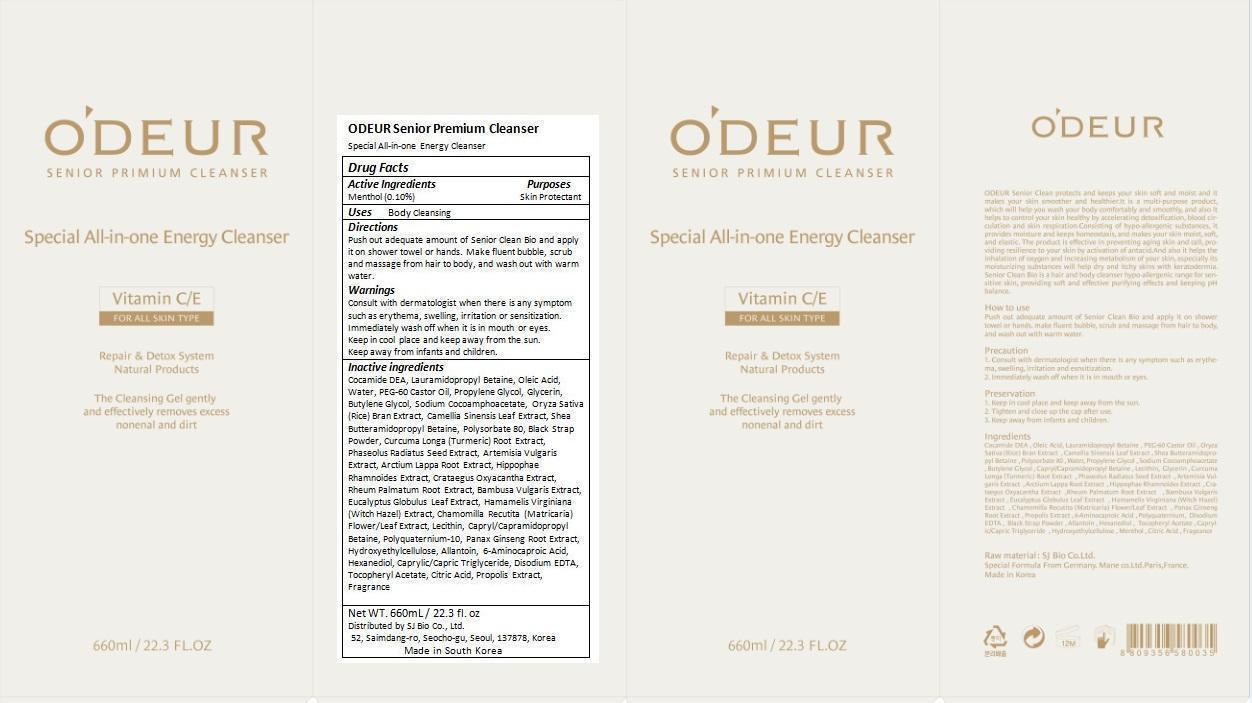 DRUG LABEL: ODEUR Senior Premium Cleanser
NDC: 69798-001 | Form: GEL
Manufacturer: SJ Bio Co., Ltd.
Category: otc | Type: HUMAN OTC DRUG LABEL
Date: 20250107

ACTIVE INGREDIENTS: MENTHOL 0.63 g/632.19 g
INACTIVE INGREDIENTS: COCO DIETHANOLAMIDE; LAURAMIDOPROPYL BETAINE; OLEIC ACID; WATER; PEG-60 CASTOR OIL; PROPYLENE GLYCOL; GLYCERIN; BUTYLENE GLYCOL; SODIUM COCOAMPHOACETATE; RICE BRAN; GREEN TEA LEAF; POLYSORBATE 80; TURMERIC; MUNG BEAN; ARTEMISIA VULGARIS ROOT; ARCTIUM LAPPA ROOT; HIPPOPHAE RHAMNOIDES FRUIT; CRATAEGUS LAEVIGATA FLOWER; RHEUM PALMATUM ROOT; BAMBUSA VULGARIS TOP; EUCALYPTUS GLOBULUS LEAF; HAMAMELIS VIRGINIANA TOP; MATRICARIA RECUTITA FLOWERING TOP; HYDROGENATED SOYBEAN LECITHIN; CAPRYL/CAPRAMIDOPROPYL BETAINE; POLYQUATERNIUM-10 (400 MPA.S AT 2%); ASIAN GINSENG; HYDROXYETHYL CELLULOSE (2000 MPA.S AT 1%); ALLANTOIN; AMINOCAPROIC ACID; HEXANEDIOL; MEDIUM-CHAIN TRIGLYCERIDES; EDETATE DISODIUM; .ALPHA.-TOCOPHEROL ACETATE; CITRIC ACID MONOHYDRATE; PROPOLIS WAX

Drug Facts

ACTIVE INGREDIENT

Menthol (0.1%)

PURPOSE

Skin Protectant

INDICATIONS AND USAGE

Body Cleansing

DOSAGE AND ADMINISTRATION

Push out adequate amount of Senior Clean Bio and apply it on shower towel or hands. Make fluent bubble, scrub and massage from hair to body, and wash out with warm water.

WARNINGS

Immediately wash off when it is in mouth or eyes.
Keep in cool place and keep away from the sun.

Keep away from infants and children.

ASK DOCTOR

Consult with doctor when there is any symptom such as erythema, swelling, irritation or sensitization.

INACTIVE INGREDIENT

Cocamide DEA, Lauramidopropyl Betaine, Oleic Acid, Water, PEG-60 Castor Oil, Propylene Glycol, Glycerin, Butylene Glycol, Sodium Cocoamphoacetate, Oryza Sativa (Rice) Bran Extract, Camellia Sinensis Leaf Extract, Shea Butteramidopropyl Betaine, Polysorbate 80, Black Strap Powder, Curcuma Longa (Turmeric) Root Extract, Phaseolus Radiatus Seed Extract, Artemisia Vulgaris Extract, Arctium Lappa Root Extract, Hippophae Rhamnoides Extract, Crataegus Oxyacantha Extract, Rheum Palmatum Root Extract, Bambusa Vulgaris Extract, Eucalyptus Globulus Leaf Extract, Hamamelis Virginiana (Witch Hazel) Extract, Chamomilla Recutita (Matricaria) Flower/Leaf Extract, Lecithin, Capryl/Capramidopropyl Betaine, Polyquaternium-10, Panax Ginseng Root Extract, Hydroxyethylcellulose, Allantoin, 6-Aminocaproic Acid, Hexanediol, Caprylic/Capric Triglyceride, Disodium EDTA, Tocopheryl Acetate, Citric Acid, Propolis Extract, Fragrance